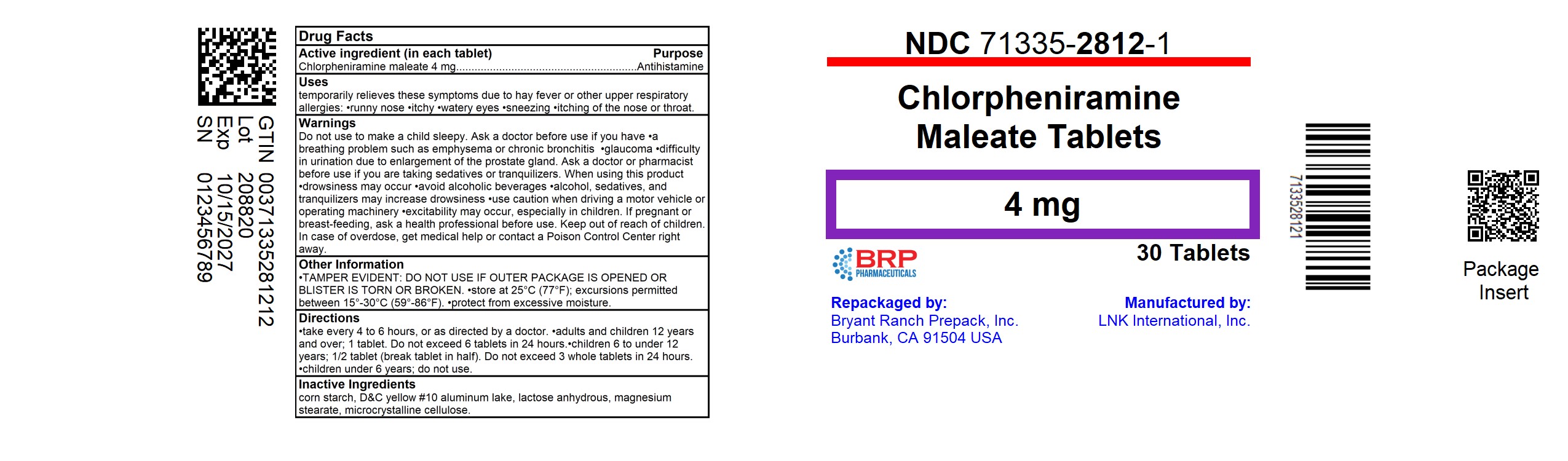 DRUG LABEL: Allergy Relief
NDC: 71335-2812 | Form: TABLET
Manufacturer: Bryant Ranch Prepack
Category: otc | Type: HUMAN OTC DRUG LABEL
Date: 20251015

ACTIVE INGREDIENTS: CHLORPHENIRAMINE MALEATE 4 mg/1 1
INACTIVE INGREDIENTS: STARCH, CORN; D&C YELLOW NO. 10 ALUMINUM LAKE; ANHYDROUS LACTOSE; MAGNESIUM STEARATE; MICROCRYSTALLINE CELLULOSE

Foster and Thrive 44-194

Active ingredient (in each tablet)

Chlorpheniramine maleate 4 mg

Purpose

Antihistamine

Uses

temporarily relieves these symptoms due to hay fever or other upper respiratory allergies:

- sneezing
- runny nose
- itchy, watery eyes
- itching of the nose or throat

Warnings

Do not use

to make a child sleepy.

Ask a doctor before use if you have

- glaucoma
- a breathing problem such as emphysema or chronic bronchitis
- difficulty in urination due to enlargement of the prostate gland

Ask a doctor or pharmacist before use if you are

taking sedatives or tranquilizers.

When using this product

- drowsiness may occur
- avoid alcoholic beverages
- use caution when driving a motor vehicle or operating machinery
- alcohol, sedatives, and tranquilizers may increase drowsiness
- excitability may occur, especially in children

If pregnant or breast-feeding,

ask a health professional before use.

Keep out of reach of children.

In case of overdose, get medical help or contact a Poison Control Center right away.

Directions

- take every 4 to 6 hours, or as directed by a doctor

adults and children 12 years and over | 1 tablet. Do not exceed 6 tablets in 24 hours.
children 6 to under 12 years | 1/2 tablet (break tablet in half). Do not exceed 3 whole tablets in 24 hours.
children under 6 years | do not use

Other information

- store at 25ºC (77ºF); excursions permitted between 15º-30ºC (59º-86ºF)
- protect from excessive moisture
- see end flap for expiration date and lot number

Inactive ingredients

corn starch, D&C yellow #10 aluminum lake, lactose anhydrous, magnesium stearate, microcrystalline cellulose

Questions or comments?

Call 833-358-6431
Monday to Friday 9:00am to 7:00pm EST

HOW SUPPLIED

Chlorpheniramine maleate 4 mg: color yellow, score 2, shape round and the imprint code 44;194.

NDC: 71335-2812-1: 30 Tablets in a BOTTLE, PLASTIC

NDC: 71335-2812-2: 60 Tablets in a BOTTLE, PLASTIC

NDC: 71335-2812-3: 100 Tablets in a BOTTLE, PLASTIC

NDC: 71335-2812-4: 120 Tablets in a BOTTLE, PLASTIC

NDC: 71335-2812-5: 40 Tablets in a BOTTLE, PLASTIC

NDC: 71335-2812-6: 24 Tablets in a BOTTLE, PLASTIC

Store at 25ºC (77ºF); excursions permitted between 15º-30ºC (59º-86ºF).
protect from excessive moisture.

Repackaged/Relabeled by:
Bryant Ranch Prepack, Inc.
Burbank, CA 91504

PACKAGE LABEL

Chlorpheniramine Maleate 4 mg Tablet